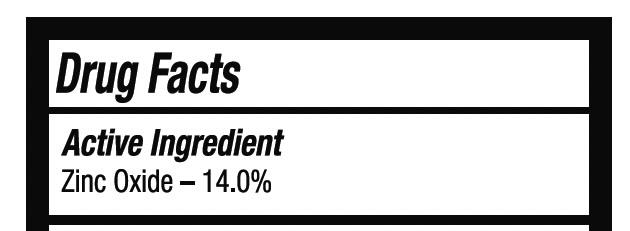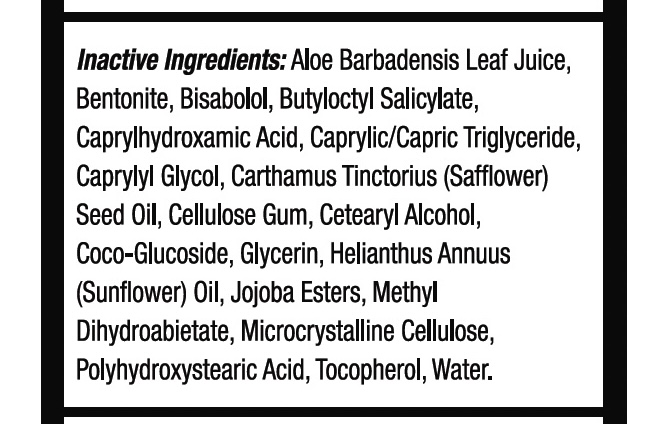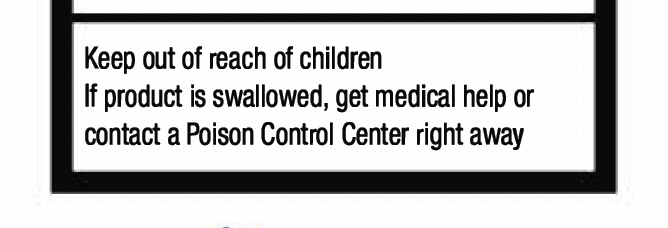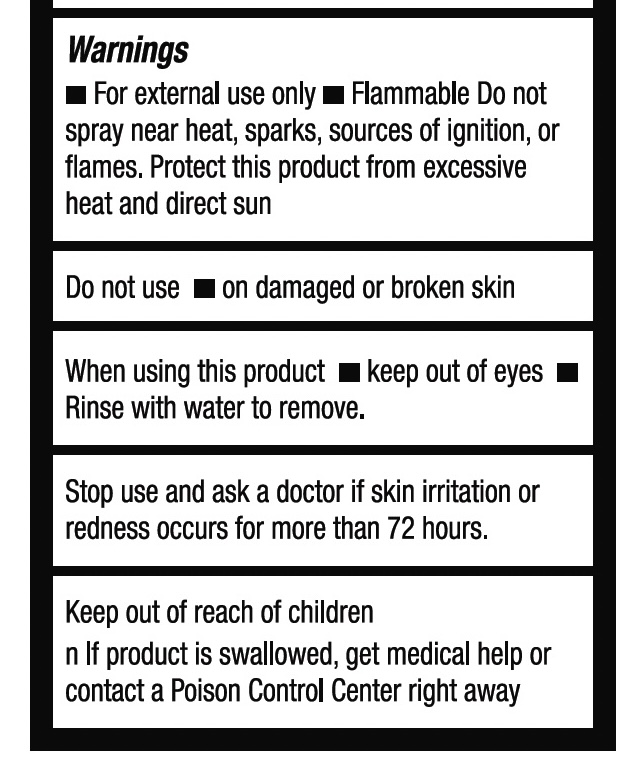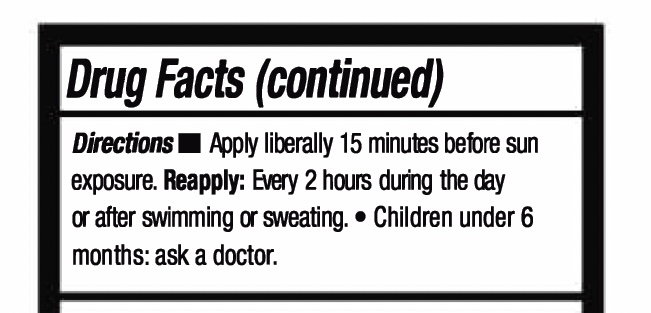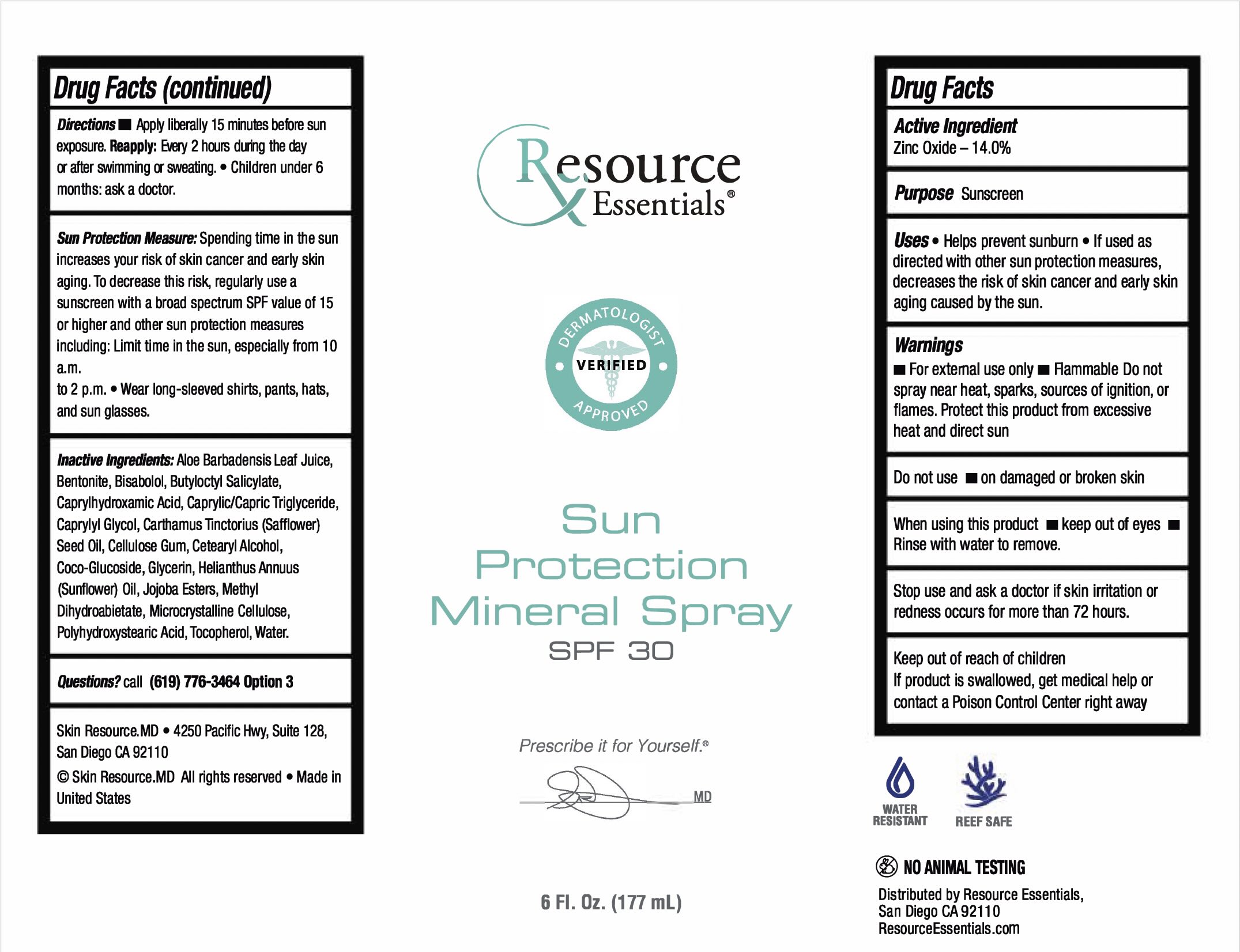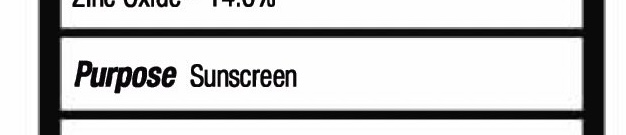 DRUG LABEL: Resource Essentials Sun Protection Mineral SPF 30
NDC: 83694-300 | Form: SPRAY
Manufacturer: Skinresource.md, L.L.C.
Category: otc | Type: HUMAN OTC DRUG LABEL
Date: 20251230

ACTIVE INGREDIENTS: ZINC OXIDE 24.78 g/177 g
INACTIVE INGREDIENTS: CARTHAMUS TINCTORIUS (SAFFLOWER) SEED OIL; HELIANTHUS ANNUUS (SUNFLOWER) SEED OIL; BISABOLOL; TOCOPHEROL; MICROCRYSTALLINE CELLULOSE; CAPRYLYL GLYCOL; CAPRYLHYDROXAMIC ACID; BUTYLOCTYL SALICYLATE; CELLULOSE GUM; CETEARYL ALCOHOL; HYDROGENATED JOJOBA OIL, RANDOMIZED; METHYL DIHYDROABIETATE; POLYHYDROXYSTEARIC ACID (2300 MW); WATER; CAPRYLIC/CAPRIC TRIGLYCERIDE; COCO-GLUCOSIDE; GLYCERIN; ALOE BARBADENSIS LEAF JUICE; BENTONITE

INDICATIONS AND USAGE

Uses • Helps prevent sunburn • If used as directed with other sun protection measures, decreases the risk of skin cancer and early skin aging caused by the sun.

Warnings

• For external use only

- Flammable Do not spray near heat, sparks, sources of ignition, or flames.
- Protect this product from excessive heat and direct sun
- Do not use on damaged or broken skin
- When using this product keep out of eyes • Rinse with water to remove.
- Stop use and ask a doctor if skin irritation or redness occurs for more than 72 hours.

Keep out of reach of children

If product is swallowed, get medical help or contact a Poison Control Center right away

Directions • Apply liberally 15 minutes before sun exposure. Reapply: Every 2 hours during the day after swimming or sweating. • Children under 6 months: ask a doctor.

Sun Protection Measure: Spending time in the sun increases your risk of skin cancer and early skin aging. To decrease this risk, regularly use a sunscreen with a broad spectrum SPF value of 15 or higher and other sun protection measures including: Limit time in the sun, especially from 10 a.m.to 2 p.m.
Wear long-sleeved shirts, pants, hats, and sun glasses

Active Ingredient Zinc Oxide - 14.0%

INACTIVE INGREDIENT

Inactive Ingredients: Aloe Barbadensis Leaf Juice, Bentonite, Bisabolol, Butyloctyl Salicylate, Caprylhydroxamic Acid, Caprylic/Capric Triglyceride, Caprylyl Glycol, Carthamus Tinctorius (Safflower)

Seed Oil, Cellulose Gum, Cetearyl Alcohol, Coco-Glucoside, Glycerin, Helianthus Annuus (Sunflower) Oil, Jojoba Esters, Methyl Dihydroabetate, Microcrystalline Cellulose, Polyhydroxystearic Acid, Tocopherol, Water.

Warnings

• For external use only - Flammable Do not spray near heat, sparks, sources of ignition, or flames. Protect this product from excessive heat and direct sun

- Do not use on damaged or broken skin
- When using this product keep out of eyes
  Rinse with water to remove.
- Stop use and ask a doctor if skin irritation or redness occurs for more than 72 hours.
- Keep out of reach of children

lf product is swallowed, get medical help or contact a Poison Control Center right away

PURPOSE

Sunscreen

Keep out of reach of children

lf product is swallowed, get medical help or contact a Poison Control Center right away

DOSAGE AND ADMINISTRATION

Directions Apply liberally 15 minutes before sun exposure. Reapply: Every 2 hours during the day or after swimming or sweating. • Children under 6 months: ask a doctor.

PACKAGE LABEL

Resource Essentials
Sun Protection Mineral Spray
SPF 30
Net Wt. 6 oz (177 mL) Resource Essentials
Sun Protection Mineral Spray
SPF 30
Net Wt. 6 oz (177 mL)